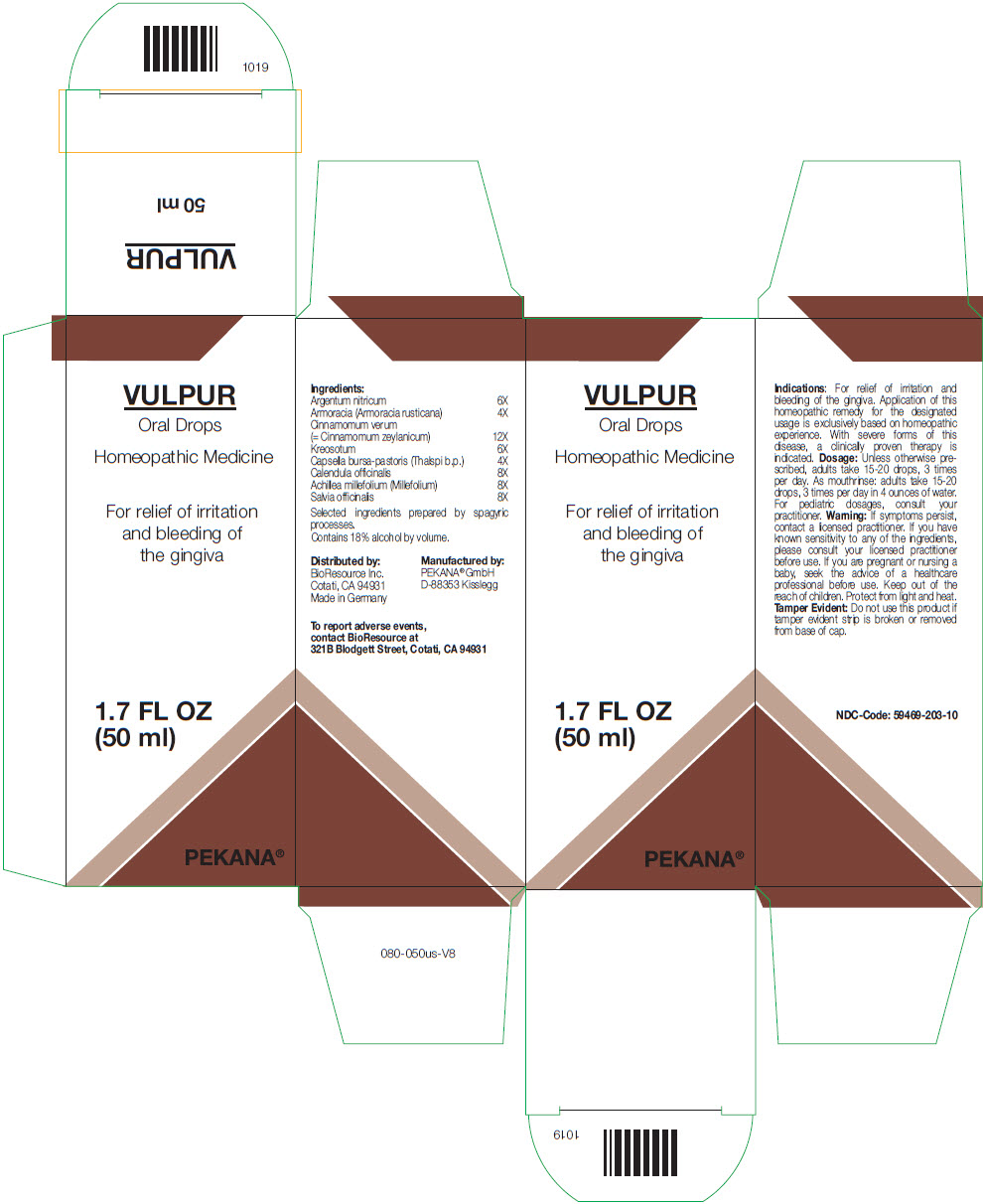 DRUG LABEL: VULPUR
NDC: 59469-203 | Form: SOLUTION/ DROPS
Manufacturer: PEKANA Naturheilmittel GmbH
Category: homeopathic | Type: HUMAN OTC DRUG LABEL
Date: 20221220

ACTIVE INGREDIENTS: Silver Nitrate 6 [hp_X]/50 mL; Armoracia rusticana whole 4 [hp_X]/50 mL; Cinnamomum verum whole 12 [hp_X]/50 mL; Wood Creosote 6 [hp_X]/50 mL; CAPSELLA BURSA-PASTORIS WHOLE 4 [hp_X]/50 mL; Calendula Officinalis Flowering Top 8 [hp_X]/50 mL; ACHILLEA MILLEFOLIUM WHOLE 8 [hp_X]/50 mL; Salvia officinalis flowering top 8 [hp_X]/50 mL
INACTIVE INGREDIENTS: Water; Alcohol

VULPUR

ACTIVE INGREDIENT

Ingredients:
Argentum nitricum | 6X
Armoracia (Armoracia rusticana) | 4X
Cinnamomum verum (= Cinnamomum zeylanicum) | 12X
Kreosotum | 6X
Capsella bursa-pastoris (Thalspi b.p.) | 4X
Calendula officinalis | 8X
Achillea millefolium (Millefolium) | 8X
Salvia officinalis | 8X

Selected ingredients prepared by spagyric processes.

INACTIVE INGREDIENT

Contains 18% alcohol by volume.

Indications

PURPOSE

For relief of irritation and bleeding of the gingiva. Application of this homeopathic remedy for the designated usage is exclusively based on homeopathic experience. With severe forms of this disease, a clinically proven therapy is indicated.

Dosage

Unless otherwise prescribed, adults take 15-20 drops, 3 times per day. As mouthrinse: adults take 15-20 drops, 3 times per day in 4 ounces of water. For pediatric dosages, consult your practitioner.

Warning

If symptoms persist, contact a licensed practitioner. If you have known sensitivity to any of the ingredients, please consult your licensed practitioner before use. If you are pregnant or nursing a baby, seek the advice of a healthcare professional before use.

Keep out of the reach of children.

STORAGE AND HANDLING

Protect from light and heat.

Tamper Evident

Do not use this product if tamper evident strip is broken or removed from base of cap.

QUESTIONS

To report adverse events, contact BioResource at 321B Blodgett Street, Cotati, CA 94931

Distributed by:
BioResource Inc.
Cotati, CA 94931

Manufactured by:
PEKANA® GmbH
D-88353 Kisslegg

PRINCIPAL DISPLAY PANEL - 50 ml Bottle Box

VULPUR
Oral Drops

Homeopathic Medicine

For relief of irritation
and bleeding of
the gingiva

1.7 FL OZ
(50 ml)

PEKANA®